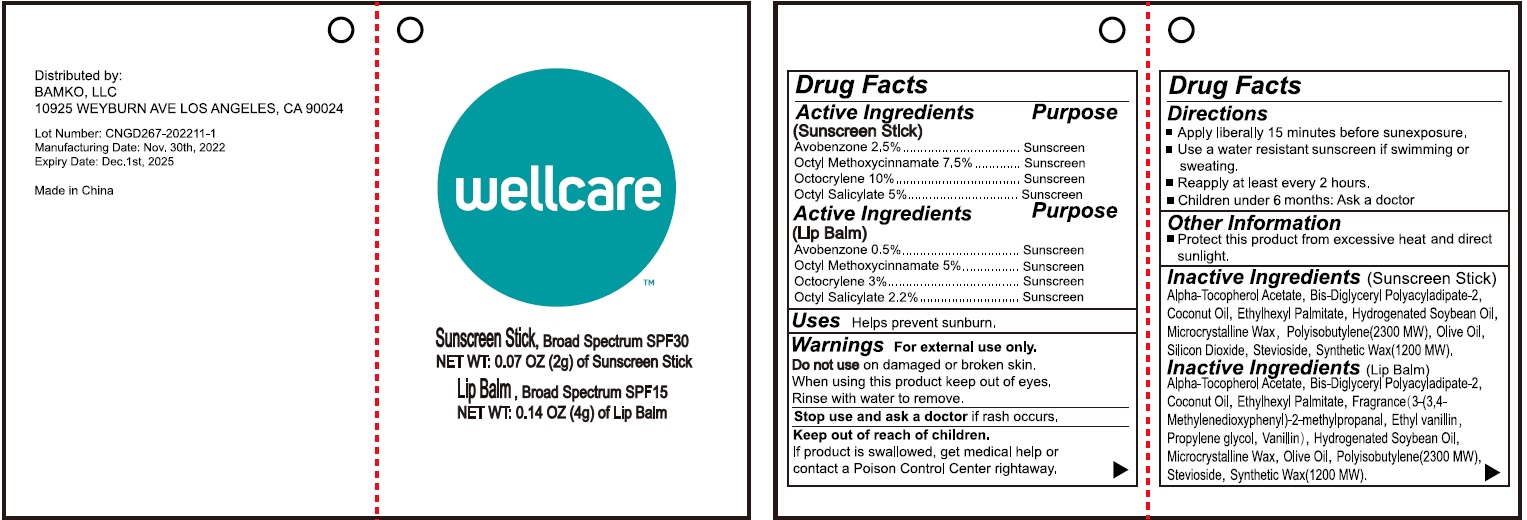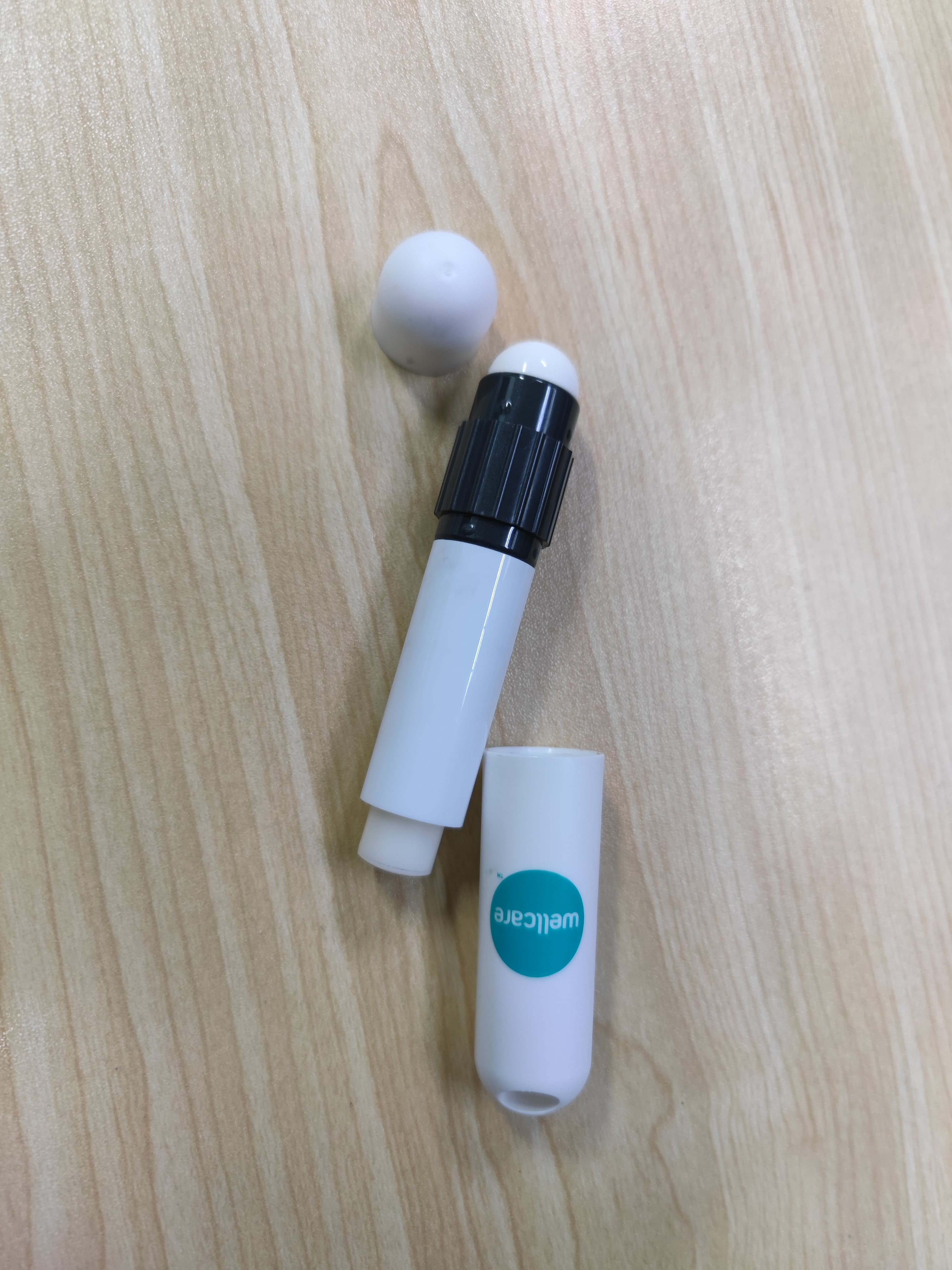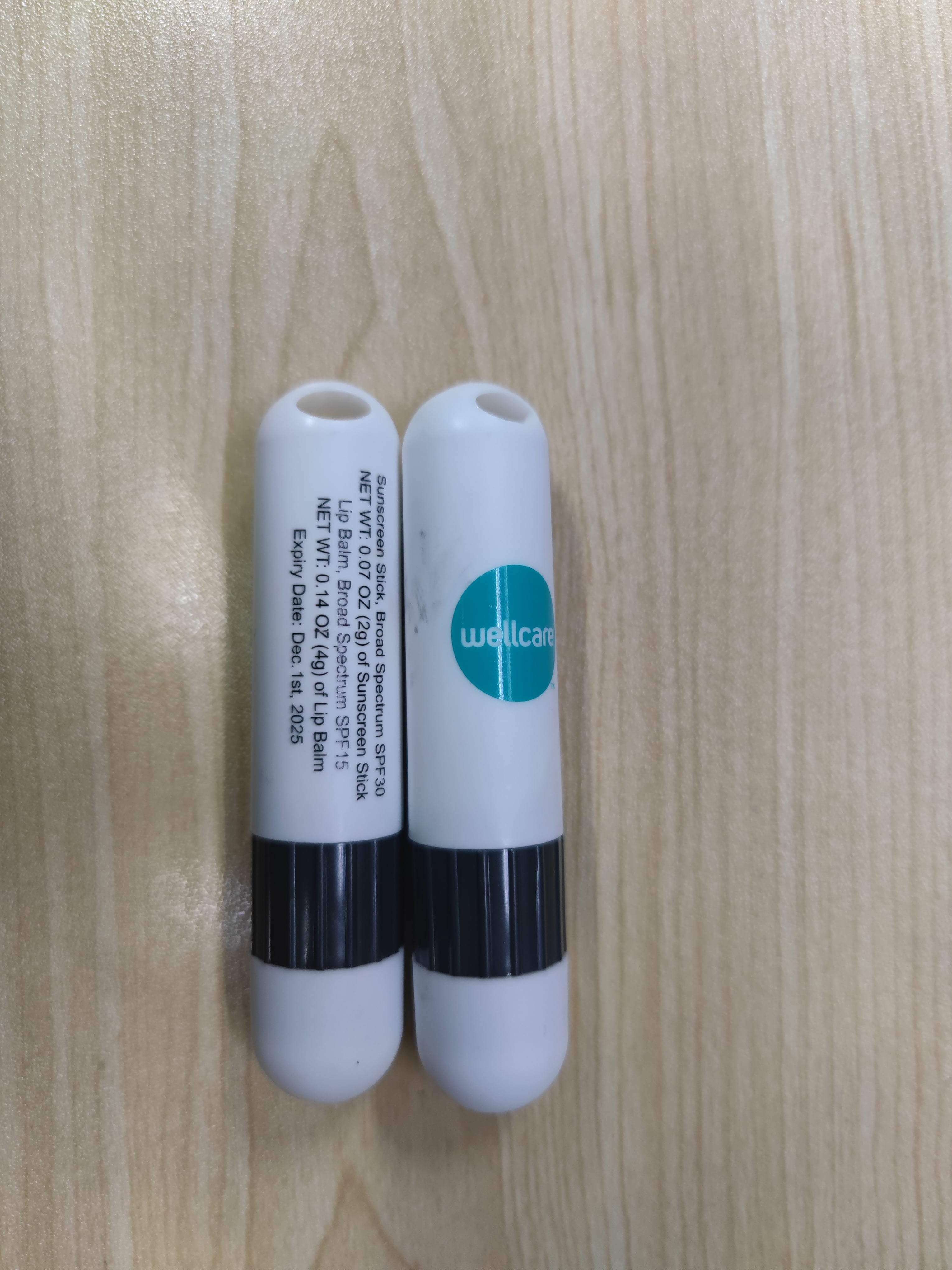 DRUG LABEL: Wellcare Sunstick Sunscreen Stick
NDC: 83149-001 | Form: STICK
Manufacturer: BAMKO, LLC
Category: otc | Type: HUMAN OTC DRUG LABEL
Date: 20260115

ACTIVE INGREDIENTS: AVOBENZONE 25 mg/1 g; OCTINOXATE 75 mg/1 g; OCTOCRYLENE 100 mg/1 g; OCTISALATE 50 mg/1 g
INACTIVE INGREDIENTS: .ALPHA.-TOCOPHEROL ACETATE; BIS-DIGLYCERYL POLYACYLADIPATE-2; COCONUT OIL; ETHYLHEXYL PALMITATE; ETHYL VANILLIN; PROPYLENE GLYCOL; VANILLIN; HYDROGENATED SOYBEAN OIL; MICROCRYSTALLINE WAX; OLIVE OIL; POLYISOBUTYLENE (2300 MW); STEVIOSIDE; SYNTHETIC WAX (1200 MW)

Wellcare Sunstick

Active Ingredient

(Sunscreen Stick) Avobenzone 2.5mg Octyl Methoxycinnamate 7.5mg Octocrylene 10mg OctyI Salicylate 5mg (Lip Balm) Avobenzone 0. 5mg. Octyl Methoxycinnamate 5mg Octocrylene 3 OctyI Salicylate 2.2mg

Purpose

Sunscreen

Uses

Helps prevent sunburn.

Warnings

For external use ony.

Do not use

on damaged or broken skin.

When using this product

keep out of eyes, Rinse with water to remove.

Stop use and ask a doctor

if rash occurs.

Keep out of reach of children.

If product is swallowed, get medical help or contact a Poison Control Center righaway.

Directions

- Apply liberally 15 minutes before sunexposure.
- Use a water resistant sunscreen if swimming or sweating.
- Reapply at least every 2 hours.
- Children under 6 months: Ask a doctor

Other Information

Protect this product from excessive heat and direct sunlight.

Inactive Ingredients

Alpha-Tocopherol Acetate, Bis-Diglyceryl Polyacyladipate-2, Coconut Oil, Ethylhexyl Palmitate, Hydrogenated Soybean Oil, Microcrystalline Wax, Polyisobutylene(2300 MW), Olive Oil, Silicon Dioxide, Stevioside, Synthetic Wax (1200 MW).

Inactive Ingredients

Alpha-Tocopherol Acetate, Bis-Diglyceryl Polyacyladipate-2, Coconut Oil, Ethylhexyl Palmitate, Fragrance (3-(3,4-Methylenedioxyphenyl)-2-methylpropanal, Ethyl vanillin, Propylene glycol, Vanillin), Hydrogenated Soybean Oil, Microcrystalline Wax, Olive Oil, Polyisobutylene(2300 MW), Stevioside, Synthetic Wax (1200 MW).